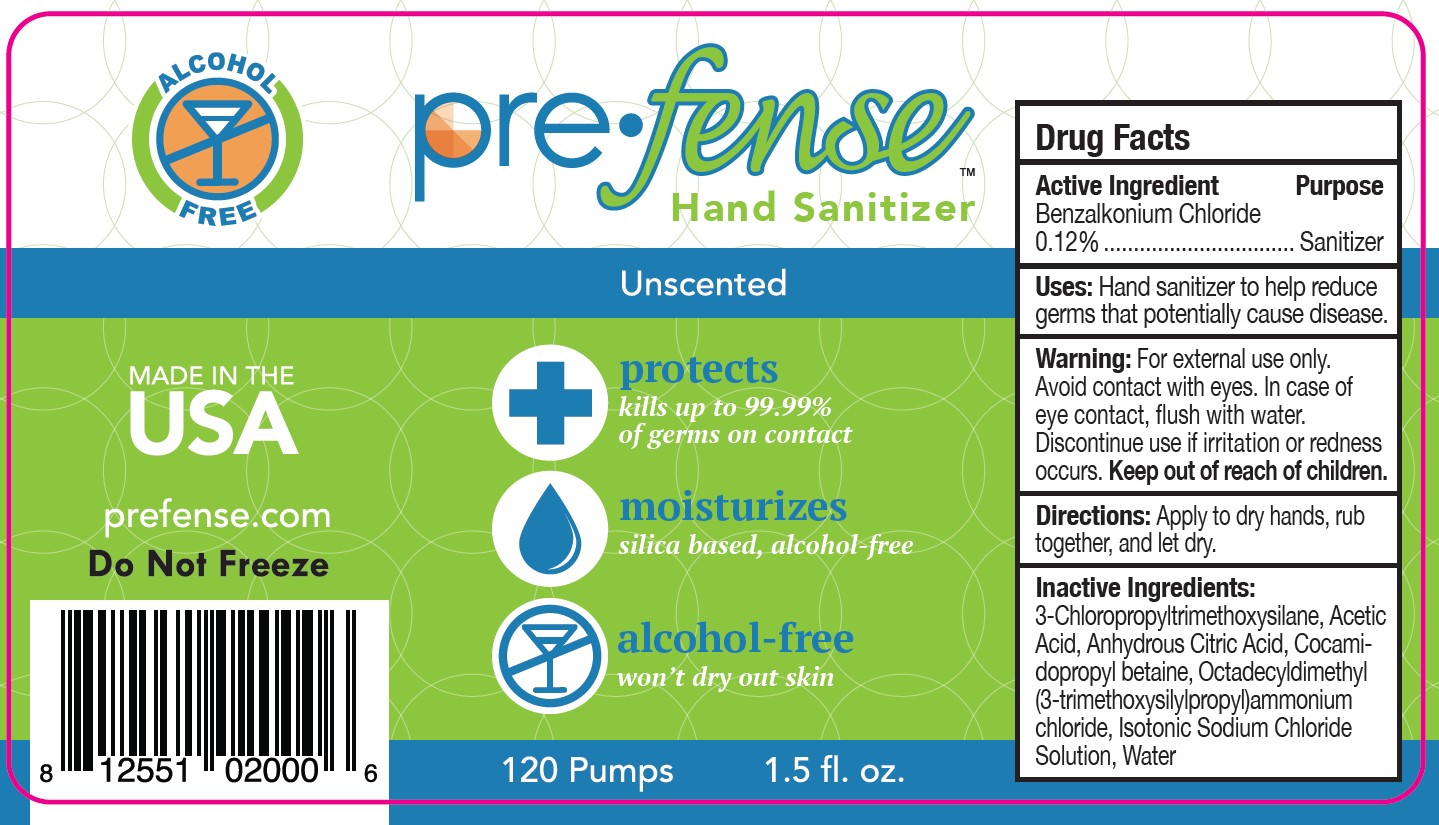 DRUG LABEL: pre fense unscented
NDC: 48404-050 | Form: LIQUID
Manufacturer: Prefense LLC
Category: otc | Type: HUMAN OTC DRUG LABEL
Date: 20251121

ACTIVE INGREDIENTS: BENZALKONIUM CHLORIDE 120 mg/100 mL
INACTIVE INGREDIENTS: ANHYDROUS CITRIC ACID; COCAMIDOPROPYL BETAINE; WATER; (3-CHLOROPROPYL)TRIMETHOXYSILANE; ISOTONIC SODIUM CHLORIDE SOLUTION; METHYL ALCOHOL; DIMETHYLOCTADECYL(3-(TRIMETHOXYSILYL)PROPYL)AMMONIUM CHLORIDE; ACETIC ACID

Prefense Unscented Hand Sanitizer

PURPOSE

Hand and Skin Sanitizer

Drug Facts

Active Ingredient

Benzalkonium Chloride ............0.12%

INDICATIONS AND USAGE

Hand sanitizer to help reduce germs that potentially cause disease.

WARNINGS

For external use only. Avoid contact with eyes. In case of eye contact, flush with water. Discontinue use if irritation or redness occurs.

Keep out of reach of children.

DOSAGE AND ADMINISTRATION

Apply to dry hands, rub together, and let dry.

INACTIVE INGREDIENT

3-Chloropropyltrimethoxysilane, Acetic Acid, Anhydrous Citric Acid, Cocomidoprophyl betaine, Octadecyldimethyl (3-trimethoxysilylpropyl)ammonium chloride, Isotonic Sodium Chloride Solution, Water

Package Label - 1.5 FL. OZ. BOTTLE LABEL

pre•fense™

Hand Sanitizer

Unscented

protects

kills up to 99.99% of germs on contact

Moisturizes

silica based, alcohol-free

alcohol-free

won't dry out skin

120 Pumps

1.5 fl. oz.